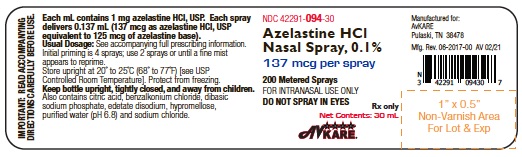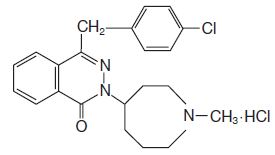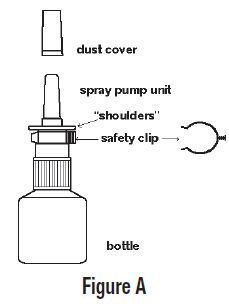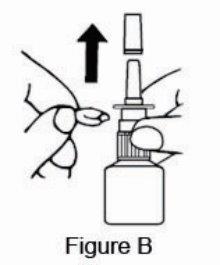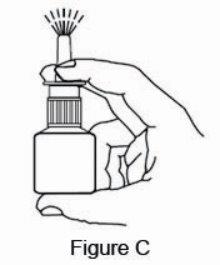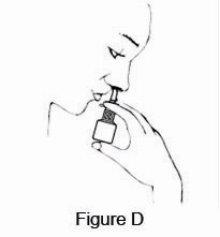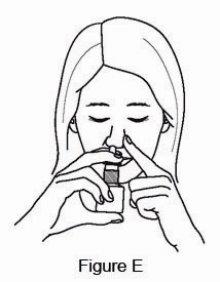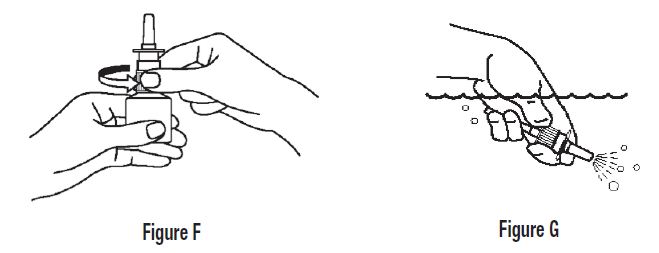 DRUG LABEL: Azelastine Hydrochloride
NDC: 42291-094 | Form: SPRAY, METERED
Manufacturer: AvKARE
Category: prescription | Type: HUMAN PRESCRIPTION DRUG LABEL
Date: 20260114

ACTIVE INGREDIENTS: AZELASTINE HYDROCHLORIDE 1 mg/1 mL
INACTIVE INGREDIENTS: BENZALKONIUM CHLORIDE; ANHYDROUS CITRIC ACID; SODIUM PHOSPHATE; EDETATE DISODIUM; HYPROMELLOSES; WATER; SODIUM CHLORIDE

HIGHLIGHTS OF PRESCRIBING INFORMATION

AZELASTINE HYDROCHLORIDE nasal spray, for intranasal use
These highlights do not include all the information needed to use AZELASTINE HYDROCHLORIDE NASAL SPRAY safely and effectively. See full prescribing information for AZELASTINE HYDROCHLORIDE NASAL SPRAY.
Initial U.S. Approval: 1996

1 INDICATIONS AND USAGE

Azelastine HCl nasal spray, 0.1% is an H1-receptor antagonist indicated for the treatment of the symptoms of seasonal allergic rhinitis in adults and pediatric patients 5 years and older and for the treatment of the symptoms of vasomotor rhinitis in adults and adolescent patients 12 years and older. (1)

2 DOSAGE AND ADMINISTRATION

- For intranasal use only. (2.3)
- Seasonal allergic rhinitis:
  - Pediatric patients 5 to 11 years of age: 1 spray per nostril twice daily. (2.1)
  - Adults and adolescents 12 years of age and older: 1 or 2 sprays per nostril twice daily. (2.1)
- Vasomotor rhinitis: 2 sprays per nostril twice daily in adults and adolescents 12 years of age and older. (2.2)
- Prime azelastine HCl nasal spray, 0.1% before initial use and when it has not been used for 3 or more days. (2.3)

3 DOSAGE FORMS AND STRENGTHS

Azelastine HCl nasal spray, 0.1%: 137 mcg of azelastine HCl, USP in each 0.137 mL spray. (3)

4 CONTRAINDICATIONS

None. (4)

5 WARNINGS AND PRECAUTIONS

- Somnolence: Avoid engaging in hazardous occupations requiring complete mental alertness such as driving or operating machinery when taking azelastine HCl nasal spray, 0.1%. (5.1)
- Alcohol and other central nervous system (CNS) depressants: Avoid concurrent use with azelastine HCl nasal spray, 0.1% because further decreased alertness and impairment of CNS performance may occur. (5.1)

6 ADVERSE REACTIONS

The most common adverse reactions (≥2% incidence) are: bitter taste, headache, somnolence, dysesthesia, rhinitis, nasal burning, pharyngitis, epistaxis, sinusitis, paroxysmal sneezing, nausea, dry mouth, fatigue, dizziness, and weight increase. (6.1)

To report SUSPECTED ADVERSE REACTIONS, contact AvKARE at 1-855-361-3993 or FDA at 1-800-FDA-1088 or www.fda.gov/medwatch.

FULL PRESCRIBING INFORMATION

1 INDICATIONS AND USAGE

Azelastine hydrochloride (HCl) nasal spray, 0.1% is indicated for the treatment of the symptoms of seasonal allergic rhinitis in adults and pediatric patients 5 years and older, and for the treatment of the symptoms of vasomotor rhinitis in adults and adolescent patients 12 years and older.

2 DOSAGE AND ADMINISTRATION

2.1 Seasonal Allergic Rhinitis

The recommended dosage of azelastine HCl nasal spray, 0.1% in adults and adolescent patients 12 years and older with seasonal allergic rhinitis is one or two sprays per nostril twice daily. The recommended dosage of azelastine HCl nasal spray, 0.1% in pediatric patients 5 years to 11 years of age is one spray per nostril twice daily.

2.2 Vasomotor Rhinitis

The recommended dosage of azelastine HCl nasal spray, 0.1% in adults and adolescent patients 12 years and older with vasomotor rhinitis is two sprays per nostril twice daily.

2.3 Important Administration Instructions

Administer azelastine HCl nasal spray, 0.1% by the intranasal route only.

Priming: Prime azelastine HCl nasal spray, 0.1% before initial use by releasing 4 sprays or until a fine mist appears. When azelastine HCl nasal spray, 0.1% has not been used for 3 or more days, reprime with 2 sprays or until a fine mist appears. Avoid spraying azelastine HCl nasal spray, 0.1% into the eyes.

3 DOSAGE FORMS AND STRENGTHS

Azelastine HCl nasal spray, 0.1% is a nasal spray solution. Each spray of azelastine HCl nasal spray, 0.1% delivers a volume of 0.137 mL solution containing 137 mcg of azelastine HCl, USP.

4 CONTRAINDICATIONS

None.

5 WARNINGS AND PRECAUTIONS

5.1 Somnolence in Activities Requiring Mental Alertness

In clinical trials, the occurrence of somnolence has been reported in some patients taking azelastine HCl nasal spray, 0.1% [see Adverse Reactions (6.1)] . Patients should be cautioned against engaging in hazardous occupations requiring complete mental alertness and motor coordination such as operating machinery or driving a motor vehicle after administration of azelastine HCl nasal spray, 0.1%. Concurrent use of azelastine HCl nasal spray, 0.1% with alcohol or other central nervous system depressants should be avoided because additional reductions in alertness and additional impairment of central nervous system performance may occur [see Drug Interactions (7.1)] .

6 ADVERSE REACTIONS

Use of azelastine HCl nasal spray, 0.1% has been associated with somnolence [see Warnings and Precautions (5.1)] .

6.1 Clinical Trials Experience

Because clinical trials are conducted under widely varying conditions, adverse reaction rates observed in clinical trials of a drug cannot be directly compared to rates in the clinical trials of another drug and may not reflect rates observed in practice.

Seasonal Allergic Rhinitis

Azelastine HCl nasal spray, 0.1% Two Sprays Per Nostril Twice Daily

Adverse experience information for azelastine HCl nasal spray, 0.1% is derived from six placebo- and active-controlled, 2-day to 8-week clinical trials which included 391 patients, 12 years of age and older, with seasonal allergic rhinitis who received azelastine HCl nasal spray, 0.1% at a dose of 2 sprays per nostril twice daily. In placebo-controlled efficacy trials, the incidence of discontinuation due to adverse reactions in patients receiving azelastine HCl nasal spray, 0.1% and vehicle placebo was 2.2% and 2.8%, respectively.

Table 1 contains adverse reactions that were reported with frequencies ≥2% in the azelastine HCl nasal spray, 0.1% 2 sprays per nostril twice daily treatment group and more frequently than placebo.

Table 1: Adverse Reactions Reported in ≥2% Incidence in Placebo-Controlled Trials in Patients with Seasonal Allergic Rhinitis [n (%)]

 | Azelastine HCl Nasal Spray, 0.1% N = 391 | Vehicle Placebo N = 353
Bitter Taste | 77 (19.7%) | 2 (0.6%)
Headache | 58 (14.8%) | 45 (12.7%)
Somnolence | 45 (11.5%) | 19 (5.4%)
Nasal Burning | 16 (4.1%) | 6 (1.7%)
Pharyngitis | 15 (3.8%) | 10 (2.8%)
Paroxysmal Sneezing | 12 (3.1%) | 4 (1.1%)
Dry Mouth | 11 (2.8%) | 6 (1.7%)
Nausea | 11 (2.8%) | 4 (1.1%)
Rhinitis | 9 (2.3%) | 5 (1.4%)
Fatigue | 9 (2.3%) | 5 (1.4%)
Dizziness | 8 (2.0%) | 5 (1.4%)
Epistaxis | 8 (2.0%) | 5 (1.4%)
Weight Increase | 8 (2.0%) | 0 (0.0%)

Azelastine HCl Nasal Spray, 0.1% One Spray Per Nostril Twice Daily

Adverse experience information for azelastine HCl nasal spray, 0.1% at a dose of one spray per nostril twice daily is derived from two placebo-controlled 2-week clinical studies which included 276 patients 12 years of age and older with seasonal allergic rhinitis. The incidence of discontinuation due to adverse reactions in patients receiving azelastine HCl nasal spray, 0.1% and vehicle placebo was 0.0% and 0.8%, respectively. Bitter taste was reported in 8.3% of patients compared to none in the placebo group. Somnolence was reported in 0.4% of patients compared to none in the placebo group.

A total of 176 patients 5 to 11 years of age were exposed to azelastine HCl nasal spray, 0.1% at a dose of 1 spray each nostril twice daily in 3 placebo-controlled studies. In these studies, adverse reactions that occurred more frequently in patients treated with azelastine HCl nasal spray, 0.1% than with placebo, and that were not represented in the adult adverse reactions table above include rhinitis/cold symptoms (17.0% vs. 9.5%), cough (11.4% vs. 8.3%), conjunctivitis (5.1% vs. 1.8%), and asthma (4.5% vs. 4.1%).

Adverse Reactions <2% in azelastine HCl nasal spray, 0.1% One or Two Sprays Per Nostril Twice Daily

The following reactions were observed infrequently (<2% and exceeding placebo incidence) in patients who received azelastine HCl nasal spray, 0.1% dosed at 1 or 2 sprays per nostril twice daily in U.S. clinical trials.

Cardiovascular: flushing, hypertension, tachycardia.

Dermatological: contact dermatitis, eczema, hair and follicle infection, furunculosis, skin laceration.

Digestive: constipation, gastroenteritis, glossitis, ulcerative stomatitis, vomiting, increased SGPT, aphthous stomatitis, diarrhea, toothache.

Metabolic and Nutritional: increased appetite.

Musculoskeletal: myalgia, temporomandibular dislocation, rheumatoid arthritis.

Neurological: hyperkinesia, hypoesthesia, vertigo.

Psychological: anxiety, depersonalization, depression, nervousness, sleep disorder, thinking abnormal.

Respiratory: bronchospasm, coughing, throat burning, laryngitis, bronchitis, dry throat, nocturnal dyspnea, nasopharyngitis, nasal congestion, pharyngolaryngeal pain, sinusitis, nasal dryness, paranasal sinus hypersecretion, post nasal drip.

Special Senses: conjunctivitis, eye abnormality, eye pain, watery eyes, taste loss.

Urogenital: albuminuria, amenorrhea, breast pain, hematuria, increased urinary frequency.

Whole Body: allergic reaction, back pain, herpes simplex, viral infection, malaise, pain in extremities, abdominal pain, pyrexia.

Vasomotor Rhinitis

Adverse experience information for azelastine HCl nasal spray, 0.1% is derived from two placebo-controlled clinical studies which included 216 patients 12 years and older with vasomotor rhinitis who received azelastine HCl nasal spray, 0.1% at a dose of 2 sprays per nostril twice daily for up to 28 days. The incidence of discontinuation due to adverse reactions in patients receiving azelastine HCl nasal spray, 0.1% and vehicle placebo was 2.8% and 2.9%, respectively.

The following adverse reactions were reported with frequencies ≥ 2% in the azelastine HCl nasal spray, 0.1% treatment group and more frequently than placebo.

Table 2: Adverse Reactions Reported in ≥2% Incidence in Placebo-Controlled Trials in Patients with Vasomotor Rhinitis [n (%)]

 | Azelastine HCl Nasal Spray, 0.1% N = 216 | Vehicle Placebo N = 210
Bitter Taste | 42 (19.4%) | 5 (2.4%)
Headache | 17 (7.9%) | 16 (7.6%)
Dysesthesia | 17 (7.9%) | 7 (3.3%)
Rhinitis | 12 (5.6%) | 5 (2.4%)
Epistaxis | 7 (3.2%) | 5 (2.4%)
Sinusitis | 7 (3.2%) | 4 (1.9%)
Somnolence | 7 (3.2%) | 2 (1.0%)

Reactions observed infrequently (<2% and exceeding placebo incidence) in patients who received azelastine HCl nasal spray, 0.1% (2 sprays/nostril twice daily) in U.S. clinical trials in vasomotor rhinitis were similar to those observed in U.S. clinical trials in seasonal allergic rhinitis.

In controlled trials involving nasal and oral azelastine HCl formulations, there were infrequent occurrences of hepatic transaminase elevations.

6.2 Postmarketing Experience

During the post approval use of azelastine HCl nasal spray, 0.1%, the following adverse reactions have been identified. Because these reactions are reported voluntarily from a population of uncertain size, it is not always possible to reliably estimate their frequency or establish a causal relationship to drug exposure. Adverse reactions reported include: anaphylaxis, application site irritation, atrial fibrillation, chest pain, confusion, dyspnea, facial edema, involuntary muscle contractions, nasal sores, palpitations, paresthesia, parosmia, pruritus, rash, disturbance or loss of sense of smell and/or taste, tolerance, urinary retention, vision abnormal and xerophthalmia.

7 DRUG INTERACTIONS

7.1 Central Nervous System Depressants

Concurrent use of azelastine HCl nasal spray, 0.1% with alcohol or other central nervous system depressants should be avoided because reductions in alertness and impairment of central nervous system performance may occur [see Warnings and Precautions (5.1)] .

8 USE IN SPECIFIC POPULATIONS

8.1 Pregnancy

Risk Summary

Limited data from post-marketing experience over decades of use with azelastine HCl nasal spray, 0.1% in pregnant women have not identified any drug associated risks of miscarriage, birth defects, or other adverse maternal or fetal outcomes. In animal reproduction studies, there was no evidence of fetal harm at oral doses approximately 5 times the clinical daily dose. Oral administration of azelastine HCl to pregnant mice, rats, and rabbits, during the period of organogenesis, produced developmental toxicity that included structural abnormalities, decreased embryo-fetal survival, and decreased fetal body weights at doses 270 times and higher than the maximum recommended human daily intranasal dose (MRHDID) of 1.096 mg. However, the relevance of these findings in animals to pregnant women was considered questionable based upon the high animal to human dose multiple.

The estimated background risk of major birth defects and miscarriage for the indicated populations is unknown. All pregnancies have a background risk of birth defect, loss, or other adverse outcomes. In the U.S. general population, the estimated background risk of major birth defects and miscarriage in clinically recognized pregnancies is 2% to 4% and 15% to 20%, respectively.

Data

Animal Data

In an embryo-fetal development study in mice dosed during the period of organogenesis, azelastine HCl caused embryo-fetal death, structural abnormalities (cleft palate; short or absent tail; fused, absent or branched ribs), delayed ossification, and decreased fetal weight at approximately 300 times the maximum recommended human daily intranasal dose (MRHDID) in adults (on a mg/m^2 basis at a maternal oral dose of 68.6 mg/kg/day), which also caused maternal toxicity as evidenced by decreased maternal body weight. Neither fetal nor maternal effects occurred in mice at approximately 15 times the MRHDID in adults (on a mg/m^2 basis at a maternal oral dose of 3 mg/kg/day).

In an embryo-fetal development study in pregnant rats dosed during the period of organogenesis from gestation days 7 to 17, azelastine HCl caused structural abnormalities (oligo-and brachydactylia), delayed ossification, and skeletal variations, in the absence of maternal toxicity, at approximately 270 times the MRHDID in adults (on a mg/m^2 basis at a maternal oral dose of 30 mg/kg/day). Azelastine HCl caused embryo-fetal death and decreased fetal weight and severe maternal toxicity at approximately 610 times the MRHDID (on a mg/m^2 basis at a maternal oral dose of 68.6 mg/kg/day). Neither fetal nor maternal effects occurred at approximately 20 times the MRHDID (on a mg/m^2 basis at a maternal oral dose of 2 mg/kg/day).

In an embryo-fetal development study in pregnant rabbits dosed during the period of organogenesis from gestation days 6 to 18, azelastine HCl caused abortion, delayed ossification and decreased fetal weight and severe maternal toxicity at approximately 530 times the MRHDID in adults (on a mg/m^2 basis at a maternal oral dose of 30 mg/kg/day). Neither fetal nor maternal effects occurred at approximately 5 times the MRHDID (on a mg/m^2 basis at a maternal oral dose of 0.3 mg/kg/day).

In a prenatal and postnatal development study in pregnant rats dosed from late in the gestation period and through the lactation period from gestation day 17 through lactation day 21, azelastine HCl produced no adverse developmental effects on pups at maternal doses up to approximately 270 times the MRHDID (on mg/m^2 basis at a maternal dose of 30 mg/kg/day).

8.2 Lactation

Risk Summary

There are no data on the presence of azelastine HCl in human milk, the effects on the breastfed infant, or the effects on milk production. Breastfed infants should be monitored for signs of milk rejection during azelastine HCl use by lactating women (see Clinical Considerations).The developmental and health benefits of breastfeeding should be considered along with the mother’s clinical need for azelastine HCl nasal spray, 0.1% and any potential adverse effects on the breastfed infant from azelastine HCl nasal spray, 0.1% or from the underlying maternal condition.

Clinical Considerations

Monitoring for Adverse Reactions
Breastfed infants of lactating women treated with azelastine HCl nasal spray, 0.1% should be monitored for possible signs of milk rejection related to the bitter taste of azelastine HCl.

8.4 Pediatric Use

The safety and effectiveness of azelastine HCl nasal spray, 0.1% for the treatment of symptoms of seasonal allergic rhinitis have been established for patients 5 years and older [see Adverse Reactions (6.1) and Clinical Studies (14.1)] . The safety and effectiveness of azelastine HCl nasal spray, 0.1% for the treatment of vasomotor rhinitis have been established for patients 12 years and older [see Adverse Reactions (6.1) and Clinical Studies (14.2)] . The safety and effectiveness of azelastine HCl nasal spray, 0.1% in pediatric patients below the age of 5 years with seasonal allergic rhinitis and in pediatric patients below the age of 12 years with vasomotor rhinitis have not been established.

8.5 Geriatric Use

Clinical trials of azelastine HCl nasal spray, 0.1% did not include sufficient numbers of patients aged 65 and over to determine whether they respond differently from younger patients. Other reported clinical experience has not identified differences in responses between the elderly and younger patients. In general, dose selection for an elderly patient should be cautious, usually starting at the low end of the dosing range, reflecting the greater frequency of decreased hepatic, renal, or cardiac function, and of concomitant disease or other drug therapy.

10 OVERDOSAGE

There have been no reported overdosages with azelastine HCl nasal spray, 0.1%. Acute overdosage by adults with this dosage form is unlikely to result in clinically significant adverse reactions, other than increased somnolence, since one bottle of azelastine HCl nasal spray, 0.1% contains 30 mg of azelastine(HCl). Clinical trials in adults with single doses of the oral formulation of azelastine (HCl) (up to 16 mg) have not resulted in increased incidence of serious adverse reactions. General supportive measures should be employed if overdosage occurs. There is no known antidote to azelastine HCl nasal spray, 0.1%. Oral ingestion of antihistamines has the potential to cause serious adverse effects in young children. Accordingly, azelastine HCl nasal spray, 0.1% should be kept out of the reach of children.

11 DESCRIPTION

Azelastine HCl nasal spray, 0.1%, 137 micrograms (mcg), is an antihistamine formulated as a metered-spray solution for intranasal administration. Azelastine HCl, USP occurs as a white, almost odorless, crystalline powder with a bitter taste. It has a molecular weight of 418.37. It is sparingly soluble in water, methanol, and propylene glycol and slightly soluble in ethanol, octanol, and glycerine. It has a melting point of about 225°C and the pH of a saturated solution is between 5.0 and 5.4. Its chemical name is (±)-1-(2H)-phthalazinone,4-[(4-chlorophenyl) methyl]-2-(hexahydro-1-methyl-1H-azepin-4-yl)-, monohydrochloride. Its molecular formula is C22H24ClN3O•HCl with the following chemical structure:

Azelastine HCl nasal spray, 0.1% contains 0.1% azelastine HCl, USP in an aqueous solution at pH 6.8 ± 0.3. It also contains benzalkonium chloride (125 mcg/mL), citric acid, dibasic sodium phosphate, edetate disodium, hypromellose, purified water (pH 6.8) and sodium chloride.

After priming [see Dosage and Administration (2.3)] , each metered spray delivers a 0.137 mL mean volume containing 137 mcg of azelastine HCl, USP (equivalent to 125 mcg of azelastine base). The bottle can deliver 200 metered sprays.

12 CLINICAL PHARMACOLOGY

12.1 Mechanism of Action

Azelastine HCl, a phthalazinone derivative, exhibits histamine H1-receptor antagonist activity in isolated tissues, animal models, and humans. Azelastine HCl nasal spray, 0.1% is administered as a racemic mixture with no difference in pharmacologic activity noted between the enantiomers in in vitro studies. The major metabolite, desmethylazelastine, also possesses H1-receptor antagonist activity.

12.2 Pharmacodynamics

Cardiac Electrophysiology:

In a placebo-controlled study (95 subjects with allergic rhinitis), there was no evidence of an effect of azelastine HCl nasal spray, 0.1% (2 sprays per nostril twice daily for 56 days) on cardiac repolarization as represented by the corrected QT interval (QTc) of the electrocardiogram. Following multiple dose oral administration of azelastine 4 mg or 8 mg twice daily, the mean change in QTc was 7.2 msec and 3.6 msec, respectively.

Interaction studies investigating the cardiac repolarization effects of concomitantly administered oral azelastine HCl and erythromycin or ketoconazole were conducted. These drugs had no effect on QTc based on analysis of serial electrocardiograms. At a dose approximately 8 times the maximum recommended dose, azelastine HCl does not prolong the QTc interval to any clinically relevant extent.

12.3 Pharmacokinetics

Absorption: After intranasal administration, the systemic bioavailability of azelastine HCl is approximately 40%. Maximum plasma concentrations (Cmax) are achieved in 2 to 3 hours.

Azelastine HCl administered intranasally at doses above two sprays per nostril twice daily for 29 days resulted in greater than proportional increases in Cmax and area under the curve (AUC) for azelastine.

Distribution: Based on intravenous and oral administration, the steady-state volume of distribution is 14.5 L/kg. In vitro studies with human plasma indicate that the plasma protein binding of azelastine and its metabolite, desmethylazelastine, are approximately 88% and 97%, respectively.

Metabolism: Azelastine is oxidatively metabolized to the principal active metabolite, desmethylazelastine, by the cytochrome P450 enzyme system. The specific P450 isoforms responsible for the biotransformation of azelastine have not been identified. After intranasal dosing of azelastine HCl to steady-state, plasma concentrations of desmethylazelastine range from 20% to 50% of azelastine concentrations. Limited data indicate that the metabolite profile is similar when azelastine HCl is administered via the intranasal or oral route.

Elimination: Based on intravenous and oral administration, the elimination half-life and plasma clearance are 22 hours and 0.5 L/h/kg, respectively. Approximately 75% of an oral dose of radiolabeled azelastine HCl was excreted in the feces with less than 10% as unchanged azelastine.

Special Populations:

Hepatic Impairment: Following oral administration, pharmacokinetic parameters were not influenced by hepatic impairment.

Renal Impairment: Based on oral, single-dose studies, renal insufficiency (creatinine clearance <50 mL/min) resulted in a 70% to 75% higher Cmax and AUC compared to normal subjects. Time to maximum concentration was unchanged.

Age: Following oral administration, pharmacokinetic parameters were not influenced by age.

Gender: Following oral administration, pharmacokinetic parameters were not influenced by gender.

Race: The effect of race has not been evaluated.

Drug-Drug Interactions:

Erythromycin: No significant pharmacokinetic interaction was observed with the co-administration of orally administered azelastine (4 mg twice daily) with erythromycin (500 mg three times daily for 7 days). In this study, co-administration of orally administered azelastine with erythromycin resulted in Cmax of 5.36 ± 2.6 ng/mL and AUC of 49.7 ± 24 ng•h/mL for azelastine, whereas, administration of azelastine alone resulted in Cmax of 5.57 ± 2.7 ng/mL and AUC of 48.4 ± 24 ng•h/mL for azelastine.

Cimetidine and Ranitidine: In a multiple-dose, steady-state drug interaction trial in healthy subjects, cimetidine (400 mg twice daily) increased orally administered mean azelastine (4 mg twice daily) concentrations by approximately 65%. No pharmacokinetic interaction was observed with co-administration of orally administered azelastine (4 mg twice daily) with ranitidine hydrochloride (150 mg twice daily). Oral co-administration of azelastine with ranitidine resulted in Cmax of 8.89 ±3.28 ng/mL and AUC of 88.22 ± 40.43 ng•h/mL for azelastine, whereas, azelastine when administered alone resulted in Cmax of 7.83 ± 4.06 ng/mL and AUC of 80.09 ± 43.55 ng•h/mL for azelastine.

Theophylline: No significant pharmacokinetic interaction was observed with the co-administration of an oral 4 mg dose of azelastine HCl twice daily and theophylline 300 mg or 400 mg twice daily.

13 NONCLINICAL TOXICOLOGY

13.1 Carcinogenesis, Mutagenesis, Impairment of Fertility

Two-year carcinogenicity studies in Crl:CD(SD)BR rats and NMRI mice were conducted to assess the carcinogenic potential of azelastine HCl. No evidence of tumorigenicity was observed in rats at doses up to 30 mg/kg (approximately 270 and 240 times the MRHDID for adults and children, respectively, on a mg/m^2 basis). No evidence for tumorigenicity was observed in mice at doses up to 25 mg/kg (approximately 110 and 100 times the MRHDID for adults and children, respectively, on a mg/m^2 basis).

Azelastine HCl showed no genotoxic effects in the Ames test, DNA repair test, mouse lymphoma forward mutation assay, mouse micronucleus test, or chromosomal aberration test in rat bone marrow.

There were no effects on male or female fertility and reproductive performance in male and female rats at oral doses up to 30 mg/kg (approximately 270 times the MRHDID in adults on a mg/m^2 basis). At 68.6 mg/kg (approximately 610 times the MRHDID on a mg/m^2 basis), the duration of estrous cycles was prolonged and copulatory activity and the number of pregnancies were decreased. The numbers of corpora lutea and implantations were decreased; however, pre-implantation loss was not increased.

14 CLINICAL STUDIES

14.1 Seasonal Allergic Rhinitis

Two Sprays Per Nostril Twice Daily

The efficacy and safety of azelastine HCl nasal spray, 0.1% were evaluated in three placebo-controlled clinical trials of azelastine HCl nasal spray, 0.1% including 322 patients with seasonal allergic rhinitis who received two sprays per nostril twice a day for up to 4 weeks. These trials included 55 pediatric patients ages 12 to 16 years. Assessment of efficacy was based on the 12-hour reflective Total Symptom Complex (TSC) and Major Symptom Complex (MSC). The MSC was calculated as the average of individual symptoms of nose blows, sneezes, runny nose/sniffles, itchy nose, and watery eyes as assessed by patients on a 0 to 5 categorical scale. Azelastine HCl nasal spray, 0.1% two sprays per nostril twice daily demonstrated a greater decrease in the MSC than placebo (Table 3).

Table 3: Mean Change from Baseline in Reflective MSC* in Adults and Adolescents ≥12 Years with Seasonal Allergic Rhinitis Treated with Azelastine HCl Nasal Spray, 0.1% Two Sprays Per Nostril Twice Daily Versus Placebo

 | Treatment | N | Baseline LS Mean (SD) | Change from Baseline (SD) | Treatment Difference | P-value
Trial 1: 12 Hour AM and PM Reflective MSC
 | Azelastine HCl Nasal Spray, 0.1% | 63 | 11.48 (4.13) | -3.05 (3.51) | 1.98 | <0.01
 | Placebo Nasal Spray | 60 | 10.84 (4.53) | -1.07 (3.52) | 1.98 | <0.01
Trial 2: 12 Hour AM and PM Reflective MSC
 | Azelastine HCl Nasal Spray, 0.1% | 63 | 12.50 (4.5) | -4.10 (3.46) | 2.03 | <0.01
 | Placebo Nasal Spray | 63 | 12.18 (4.64) | -2.07 (4.01) | 2.03 | <0.01
Trial 3: 12 Hour AM and PM Reflective MSC
 | Azelastine HCl Nasal Spray, 0.1% | 66 | 12.04 (4.03) | -3.31 (3.74) | 1.35 | 0.04
 | Placebo Nasal Spray | 66 | 11.66 (3.96) | -1.96 (3.57) | 1.35 | 0.04
* Major Symptom Complex (MSC): Average of individual symptoms of nose blows, sneezes, runny nose/sniffles, itchy nose, and watery eyes as assessed by patients on a 0 to 5 categorical scale.

In dose-ranging trials, administration of azelastine HCl nasal spray, 0.1% two sprays per nostril twice daily resulted in a statistically significant decrease in symptoms compared to saline placebo within 3 hours after initial dosing and persisted over the 12-hour dosing interval.

One Spray Per Nostril Twice Daily

The efficacy and safety of azelastine HCl nasal spray, 0.1% were evaluated in two placebo-controlled clinical trials of azelastine HCl nasal spray, 0.1% including 275 patients with seasonal allergic rhinitis who received one spray per nostril twice a day for up to 2 weeks. Assessment of efficacy was based on the 12-hour reflective Total Nasal Symptom Score [rTNSS]. rTNSS is calculated as the sum of the patients scoring of four individual nasal symptoms (runny nose, sneezing, itchy nose, and nasal congestion) as assessed by patients on a 0 to 3 categorical scale. The primary efficacy endpoint was the change from Baseline to Day 14 in rTNSS. The mean change from baseline in rTNSS was greater in patients receiving azelastine HCl nasal spray, 0.1% one spray per nostril twice daily than those receiving placebo (Table 4).

Table 4: Mean Change from Baseline in Reflective TNSS* in Adults and Adolescents ≥12 years with Seasonal Allergic Rhinitis Treated with Azelastine HCl Nasal Spray, 0.1% One Spray Per Nostril Twice Daily Versus Placebo

 | Treatment | N | Baseline LS Mean (SD) | Change from Baseline (SD) | Treatment Difference | P-value
Trial 4: 12 Hour AM and PM Reflective TNSS
 | Azelastine HCl Nasal Spray, 0.1% | 138 | 16.34 (4.22) | -2.69 (4.79) | 1.38 | 0.01
 | Placebo Nasal Spray | 141 | 17.21 (4.32) | -1.31 (4.29) | 1.38 | 0.01
Trial 5: 12 Hour AM and PM Reflective TNSS
 | Azelastine HCl Nasal Spray, 0.1% | 137 | 16.62 (4.20) | -3.68 (4.16) | 1.18 | 0.02
 | Placebo Nasal Spray | 136 | 16.84 (4.77) | -2.50 (4.01) | 1.18 | 0.02
* Total Nasal Symptom Score (TNSS): Average of individual symptoms of runny nose, sneezing, itchy nose, and nasal congestion as assessed by patients on a 0 to 3 categorical scale.

Two-week studies comparing the efficacy (and safety) of azelastine HCl nasal spray, 0.1% two sprays per nostril twice daily versus one spray per nostril twice daily were not conducted.

14.2 Vasomotor Rhinitis

The efficacy and safety of azelastine HCl nasal spray, 0.1% were evaluated in two placebo-controlled clinical trials of azelastine HCl nasal spray, 0.1% including 216 patients with vasomotor rhinitis who received two sprays per nostril twice a day for up to 4 weeks. These patients had vasomotor rhinitis for at least one year, negative skin tests to indoor and outdoor aeroallergens, negative nasal smears for eosinophils, and negative sinus X-rays. Azelastine HCl nasal spray, 0.1% demonstrated a significantly greater decrease in a symptom complex comprised of rhinorrhea, post nasal drip, nasal congestion, and sneezing compared to placebo.

16 HOW SUPPLIED/STORAGE AND HANDLING

Azelastine HCl nasal spray 0.1%, 137 mcg, is supplied as a 30-mL package (NDC 42291-094-30) delivering 200 metered sprays in a high-density polyethylene (HDPE) bottle fitted with a metered-dose spray pump unit.

The spray pump unit consists of a nasal spray pump fitted with a white safety clip and a white or clear plastic dust cover. The net content of the bottle is 30 mL (net weight 30 g of solution). Each bottle contains 30 mg (1 mg/mL) of azelastine HCl, USP. After priming [see Dosage and Administration (2.3)] , each spray delivers a fine mist containing a mean volume of 0.137 mL solution containing 137 mcg of azelastine HCl, USP. The correct amount of medication in each spray cannot be assured before the initial priming and after 200 sprays have been used, even though the bottle is not completely empty.

The bottle should be discarded after 200 sprays have been used. Azelastine HCl nasal spray, 0.1% should not be used after the expiration date “EXP” printed on the medicine label and carton.

Storage:

Store upright at 20° to 25°C (68° to 77°F) [see USP Controlled Room Temperature]. Protect from freezing.

17 PATIENT COUNSELING INFORMATION

See FDA-approved patient labeling (Patient Information and Instructions for Use).

Activities Requiring Mental Alertness

Somnolence has been reported in some patients taking azelastine HCl nasal spray, 0.1%. Caution patients against engaging in hazardous occupations requiring complete mental alertness and motor coordination such as driving or operating machinery after administration of azelastine HCl nasal spray, 0.1% [see Warnings and Precautions (5.1)] .

Concurrent Use of Alcohol and other Central Nervous System Depressants

Instruct patients to avoid concurrent use of azelastine HCl nasal spray, 0.1% with alcohol or other central nervous system depressants because additional reductions in alertness and additional impairment of central nervous system performance may occur [see Warnings and Precautions (5.1)] .

Common Adverse Reactions

Inform patients that the treatment with azelastine HCl nasal spray, 0.1% may lead to adverse reactions, which include bitter taste, headache, somnolence, dysesthesia, rhinitis, nasal burning, pharyngitis, epistaxis, sinusitis, paroxysmal sneezing, nausea, dry mouth, fatigue, dizziness, and weight increase [see Adverse Reactions (6.1)] .

Priming

Instruct patients to prime the pump before initial use and when azelastine HCl nasal spray, 0.1% has not been used for 3 or more days [see Dosage and Administration (2.3)] .

Keep Spray Out of Eyes

Instruct patients to avoid spraying azelastine HCl nasal spray, 0.1% into their eyes.

Keep Out of Children’s Reach

Instruct patients to keep azelastine HCl nasal spray, 0.1% out of the reach of children. If a child accidentally ingests azelastine HCl nasal spray, 0.1%, seek medical help or call a poison control center immediately.

Manufactured for:

AvKARE

Pulaski, TN 38478

Manufactured by:

Amneal Pharmaceuticals LLC

Branchburg, NJ 08876

Mfg. Rev. 10-2018-02 AV 02/21

PATIENT INFORMATION

Azelastine Hydrochloride (ay” ze las’ teen hye” droe klor’ ide) Nasal Spray, 0.1%

Important: For use in your nose only.

What is azelastine HCl nasal spray, 0.1%?

- Azelastine HCl nasal spray, 0.1% is a prescription medicine used to treat symptoms of seasonal allergic rhinitis in people age 5 and older and vasomotor rhinitis in people age 12 and older.
- Azelastine HCl nasal spray, 0.1% may help to reduce your nasal symptoms including stuffy nose, runny nose, itching and sneezing.

It is not known if azelastine HCl nasal spray, 0.1% is safe and effective in children with seasonal allergic rhinitis under 5 years of age or in children with vasomotor rhinitis under 12 years of age.

What should I tell my healthcare provider before using azelastine HCl nasal spray, 0.1%?

Before using azelastine HCl nasal spray, 0.1%, tell your healthcare provider if you are:

- allergic to any of the ingredients in azelastine HCl nasal spray, 0.1%. See the end of this leaflet for a complete list of ingredients in azelastine HCl nasal spray, 0.1%.
- pregnant, or plan to become pregnant.
- breastfeeding, or plan to breastfeed. It is not known if azelastine HCl passes into your breast milk. You and your healthcare provider should decide if you will use azelastine HCl nasal spray, 0.1% if you plan to breastfeed.

Tell your healthcare provider about all the medicines you take, including prescription and over-the-counter medicines, vitamins, and herbal supplements. Azelastine HCl nasal spray, 0.1% and other medicines may affect each other, causing side effects.

How should I use azelastine HCl nasal spray, 0.1%?

- Read the Instructions for Use at the end of this leaflet for information about the right way to use azelastine HCl nasal spray, 0.1%.
- Spray azelastine HCl nasal spray, 0.1% in your nose only. Do not spray it into your eyes or mouth.
- Use azelastine HCl nasal spray, 0.1% exactly as your healthcare provider tells you to use it.
- Do not use more than your healthcare provider tells you.
- Throw away your azelastine HCl nasal spray, 0.1% bottle after using 200 sprays. Even though the bottle may not be completely empty, you may not get the correct dose of medicine.
- If you use too much or a child accidentally swallows azelastine HCl nasal spray, 0.1%, call your healthcare provider or go to the nearest hospital emergency room right away.

What should I avoid while using azelastine HCl nasal spray, 0.1%?

Azelastine HCl nasal spray, 0.1% can cause sleepiness:

- Do not drive, operate machinery, or do other dangerous activities until you know how azelastine HCl nasal spray, 0.1% affects you.
- Do not drink alcohol or take other medicines that may cause you to feel sleepy while using azelastine HCl nasal spray, 0.1%. It may make your sleepiness worse.

What are the possible side effects of azelastine HCl nasal spray, 0.1%?

The most common side effects of azelastine HCl nasal spray, 0.1% include:

- unusual bitter taste
- headache
- sleepiness
- nose burning, pain or discomfort
- runny nose
- scratchy or sore throat
- nosebleeds
- inflammation or swelling of the sinuses
- sneezing
- nausea
- dry mouth
- fatigue
- dizziness
- weight increase

Tell your healthcare provider if you have any side effect that bothers you or that does not go away.

These are not all of the possible side effects of azelastine HCl nasal spray, 0.1%. For more information, ask your healthcare provider or pharmacist.

Call your doctor for medical advice about side effects. You may report side effects to FDA at 1-800-FDA-1088.

How should I store azelastine HCl nasal spray, 0.1%?

- Keep azelastine HCl nasal spray, 0.1% upright at 68° to 77°F (20° to 25°C).
- Do not freeze azelastine HCl nasal spray, 0.1%.
- Do not use azelastine HCl nasal spray, 0.1% after the expiration date “EXP” on the medicine label and box.

Keep azelastine HCl nasal spray, 0.1% and all medicines out of reach of children.

General information about the safe and effective use of azelastine HCl nasal spray, 0.1%.

Medicines are sometimes prescribed for conditions other than those listed in a Patient Information leaflet. Do not use azelastine HCl nasal spray, 0.1% for a condition for which it was not prescribed. Do not give azelastine HCl nasal spray, 0.1% to other people, even if they have the same symptoms that you have. It may harm them.

This Patient Information leaflet summarizes the most important information about azelastine HCl nasal spray, 0.1%. If you would like more information, talk with your healthcare provider. You can ask your pharmacist or healthcare provider for information about azelastine HCl nasal spray, 0.1% that is written for health professionals.

For more information call 1-855-361-3993.

What are the ingredients in azelastine HCl nasal spray, 0.1%?

Active ingredient: Azelastine HCl, USP

Inactive ingredients: Benzalkonium chloride, citric acid, dibasic sodium phosphate, edetate disodium, hypromellose, purified water (pH 6.8) and sodium chloride.

* Trademarks are the property of their respective owners.

Manufactured for:

AvKARE

Pulaski, TN 38478

Manufactured by:

Amneal Pharmaceuticals LLC

Branchburg, NJ 08876

Mfg. Rev. 10-2018-02 AV 02/21

Instructions for Use

Azelastine Hydrochloride (ay” ze las’ teen hye” droe klor’ ide) Nasal Spray, 0.1%

Important: For use in your nose only.

For the correct dose of medicine:

- Keep your head tilted downward when spraying into your nostril.
- Change nostrils each time you use the spray.
- Breathe gently and do not tip your head back after using the spray. This will keep the medicine from running down into your throat. You may get a bitter taste in your mouth.

Figure A identifies the parts of your azelastine HCl nasal spray, 0.1% pump

Before you use azelastine HCl nasal spray, 0.1% for the first time, you will need to prime the bottle.

Priming your azelastine HCl nasal spray, 0.1%

Remove the dust cover over the tip of the pump and the white safety clip just under the “shoulders” of the pump (See Figure B).

Hold the bottle upright with 2 fingers on the shoulders of the spray pump unit and

- put your thumb on the bottom of the bottle. Press upward with your thumb and release for the pumping action. Repeat this until you see a fine mist (See Figure C).
- To get a fine mist you must pump the spray fast and use firm pressure against the bottom of the bottle. If you see a stream of liquid, the pump is not working correctly and you may have nasal discomfort.
- This should happen in 4 sprays or less.

Now your pump is primed and ready to use.

- Do not use azelastine HCl nasal spray, 0.1% unless you see a fine mist after you do the priming sprays. If you do not see a fine mist, clean the tip of the spray nozzle. See the “Cleaning the Spray Tip of your azelastine HCl nasal spray, 0.1%” section below.
- If you do not use azelastine HCl nasal spray, 0.1% for 3 or more days, you will need to prime the pump with 2 sprays or until you see a fine mist.
  Using your azelastine HCl nasal spray, 0.1%

Step 1. Blow your nose to clear your nostrils.

Step 2. Keep your head tilted downward toward your toes.

Step 3. Place the spray tip about ¼ inch to ½ inch into 1 nostril. Hold bottle upright and aim the

spray tip toward the back of your nose (See Figure D).

Step 4. Close your other nostril with a finger. Press the pump 1 time and sniff gently at the same time, keeping your head tilted forward and down (See Figure E).

Step 5. Repeat Step 3 and Step 4 in your other nostril.

Step 6. If your healthcare provider tells you to use 2 sprays in each nostril, repeat Steps 2 through 4 above for the second spray in each nostril.

Step 7. Breathe in gently, and do not tilt your head back after using azelastine HCl nasal spray, 0.1%. This will help to keep the medicine from going into your throat.

Step 8. When you finish using your azelastine HCl nasal spray, 0.1%, wipe the spray tip with a clean tissue or cloth. Put the safety clip and dust cover back on the bottle.

Cleaning the Spray Tip of your azelastine HCl nasal spray, 0.1%

- The spray tip opening is clogged, do not use a pin or pointed object to unclog the tip. Unscrew the spray pump unit from the bottle by turning it to the left (counter-clockwise) (See Figure F).
- Soak only the spray pump unit in warm water. Squirt the spray unit several times while holding it under water. Use the pumping action to clear the opening in the tip (See Figure G).

- Let the spray pump unit air dry. Make sure it is dry before you put it back onto the bottle.
- Put the spray pump unit back into the open bottle and tighten it by turning clockwise (to the right).
- To keep the medicine from leaking out, use firm pressure when you put the pump back onto the bottle.
- After cleaning, follow the instructions for priming.

This Patient Information and Instructions for Use has been approved by the U.S. Food and Drug Administration.

Manufactured for:

AvKARE

Pulaski, TN 38478

Manufactured by:

Amneal Pharmaceuticals LLC

Branchburg, NJ 08876

Mfg. Rev. 10-2018-02 AV 02/21